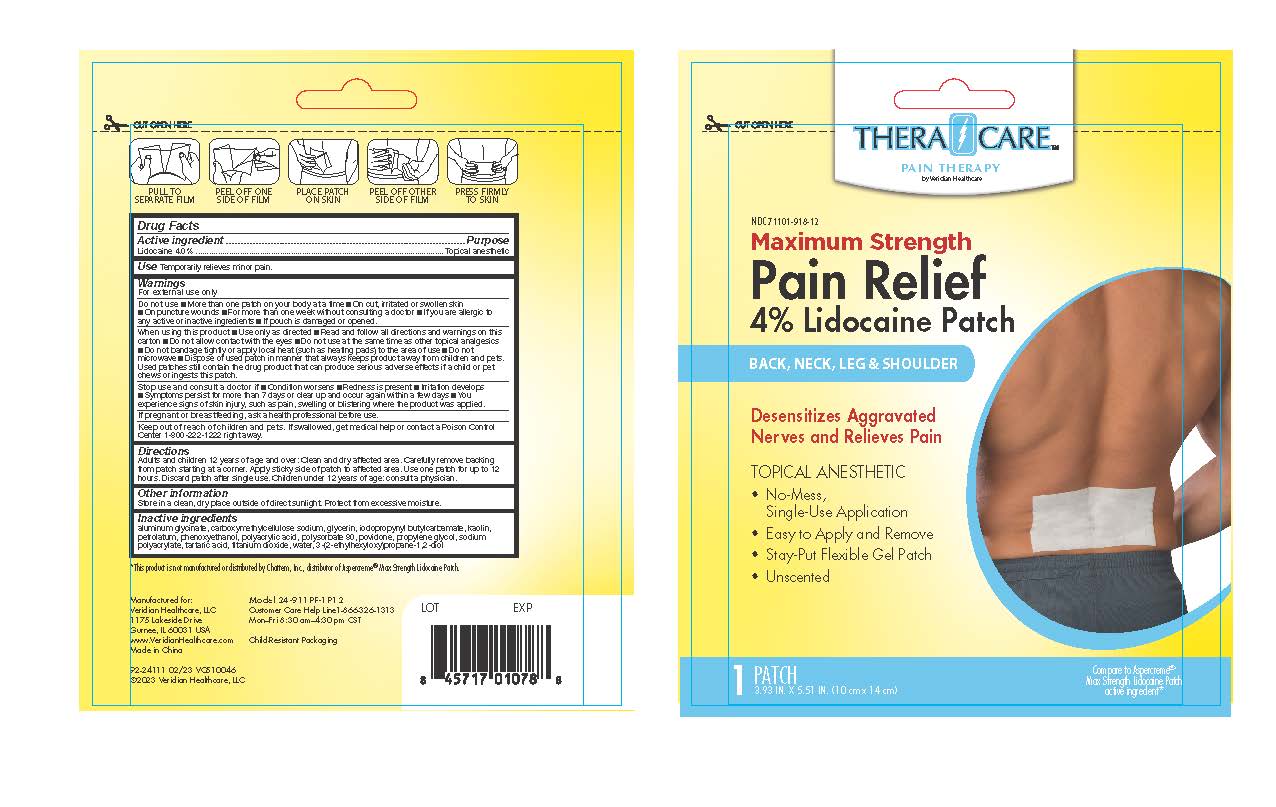 DRUG LABEL: TheraCare Pain Relieving Patch with Lidocaine
NDC: 71101-918 | Form: PATCH
Manufacturer: Veridian Healthcare
Category: otc | Type: HUMAN OTC DRUG LABEL
Date: 20241218

ACTIVE INGREDIENTS: LIDOCAINE 4 g/100 g
INACTIVE INGREDIENTS: GLYCERIN; POLYSORBATE 80; PROPYLENE GLYCOL; POVIDONE; ETHYLHEXYLGLYCERIN; TARTARIC ACID; KAOLIN; IODOPROPYNYL BUTYLCARBAMATE; WATER; POLYACRYLIC ACID (8000 MW); CARBOXYMETHYLCELLULOSE SODIUM; SODIUM POLYACRYLATE (8000 MW); DIHYDROXYALUMINUM AMINOACETATE; TITANIUM DIOXIDE; PETROLATUM; PHENOXYETHANOL

TheraCare Pain Relieving Patch with Lidocaine

Active Ingredients

Lidocaine 4%

Purpose

Topical anesthetic

Use

Temporary relieves minor pain

Warnings

For external use only

Do not use

- more than 1 patch on your body at a time
- on cut, irritated or swollen skin
- On puncture wounds
- For more than one week without consulting a doctor
- If you are allergic to any active or inactive ingredients
- if pouch is damaged or opened

When using this product

- Use only as directed
- Read and follow all directions and warnings on this carton
- Do not allow contact with the eyes
- Do not use at the same time as other topical analgesics
- Do not bandage tightly or apply local heat (such as heating pads) to the area of use
- Do not microwave
- Dispose of used patch in manner that always keeps product away from children or pets. Used patches still contain the drug product that can produce serious adverse effects if a child or pet chews or ingests this patch.

Stop use and ask a doctor if

- condition worsens
- redness is present
- irritation develops
- symptoms persist for more than 7 days or clear up and occur again within a few days
- you experience signs of skin injury, such as pain, swelling, or blistering where the product was applied

If pregnant or breast feeding

ask a health professional before use.

Keep out of reach of children and pets

If swallowed, get medical help or contact a Poison Control Center 1-800-222-1222 right away.

Directions

adults and children 12 years of age and over:

- clean and dry affected area
- carefully remove backing from patch starting at the corner
- Apply sticky side of patch to affected area.
- Use one patch for up to 12 hours.
- Discard patch after single use

children under 12 years or age: consult a physician

Other Information

Store in a clean, dry place outside of direct sunlight. Protect from excessive moisture

Inactive Ingredients

aluminum glycinate, carboxymethylcellulose sodium, glycerin, iodopropynyl butylcarbamate, kaolin, petrolatum, phenoxyethanol, polyacrylic acid, polysorbate 80, povidone, propylene glycol, sodium polyacrylate, tartaric acid, titanium dioxide, water, 3-(2-ethylhexyloxy)propane-1,2-diol